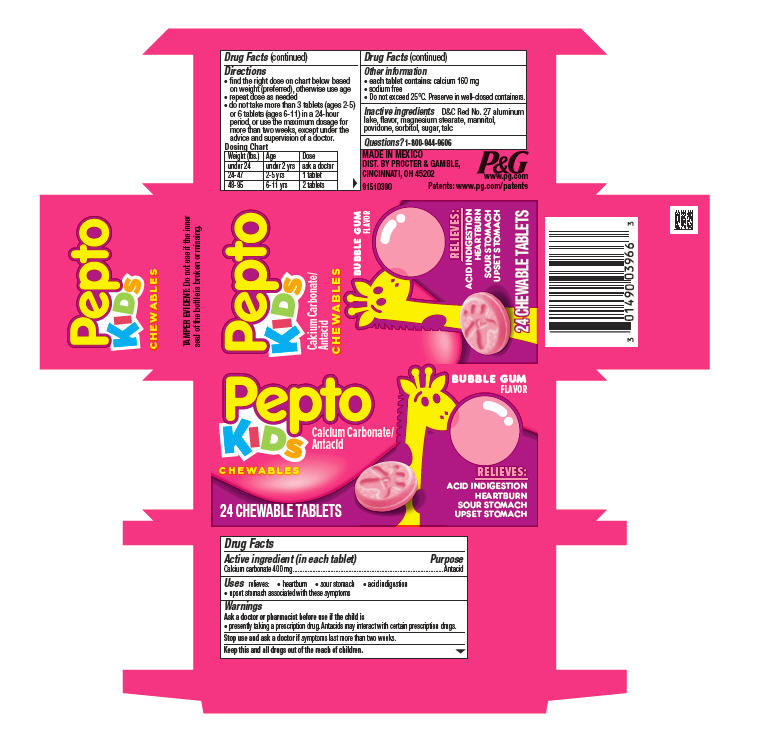 DRUG LABEL: Pepto
NDC: 58933-446 | Form: TABLET, CHEWABLE
Manufacturer: Procter & Gamble Manufactura S de RL de CV
Category: otc | Type: HUMAN OTC DRUG LABEL
Date: 20251001

ACTIVE INGREDIENTS: CALCIUM CARBONATE 400 mg/1 1
INACTIVE INGREDIENTS: D&C RED NO. 27 ALUMINUM LAKE; MAGNESIUM STEARATE; MANNITOL; POVIDONE; SORBITOL; SUCROSE; TALC

Pepto® Kids Chewable Tablets

Drug Facts

Active ingredient (in each tablet)

Calcium carbonate 400 mg

Purpose

Antacid

Uses

relieves:

- heartburn
- sour stomach
- acid indigestion
- upset stomach associated with these symptoms

Ask a doctor or pharmacist before use if the child is

- presently taking a prescription drug. Antacids may interact with certain prescription drugs.

Stop use and ask a doctor if

symptoms last more than two weeks.

KEEP OUT OF REACH OF CHILDREN

Keep this and all drugs out of the reach of children.

Directions

- find the right dose on chart below based on weight (preferred), otherwise use age
- repeat dose as needed
- do not take more than 3 tablets (ages 2-5) or 6 tablets (ages 6-11) in a 24-hour period, or use the maximum dosage for more than two weeks, except under the advice and supervision of a doctor.

Dosing Chart

Weight (lbs.) | Age | Dose
under 24 | under 2 yrs | ask a doctor
24-47 | 2-5 yrs | 1 tablet
48-95 | 6-11 yrs | 2 tablets

Other information

- each tablet contains:calcium 160 mg
- sodium free
- Do not exceed 25°C. Preserve in well-closed containers.

Inactive ingredients

D&C Red No. 27 aluminum lake, flavor, magnesium stearate, mannitol, povidone, sorbitol, sugar, talc

Questions?

1-800-944-9606

TAMPER EVIDENT: Do not use if inner printed seal on bottle is broken or missing.

MADE IN MEXICO
DIST. BY PROCTER & GAMBLE,
CINCINNATI, OH 45202

PRINCIPAL DISPLAY PANEL - 24 Tablet Carton

Pepto®

KIDS

CALCIUM CARBONATE/ANTACID

CHEWABLES

BUBBLE GUM

FLAVOR

RELIEVES:

ACID INDIGESTION

HEARTBURN
SOUR STOMACH
UPSET STOMACH

24 CHEWABLE TABLETS